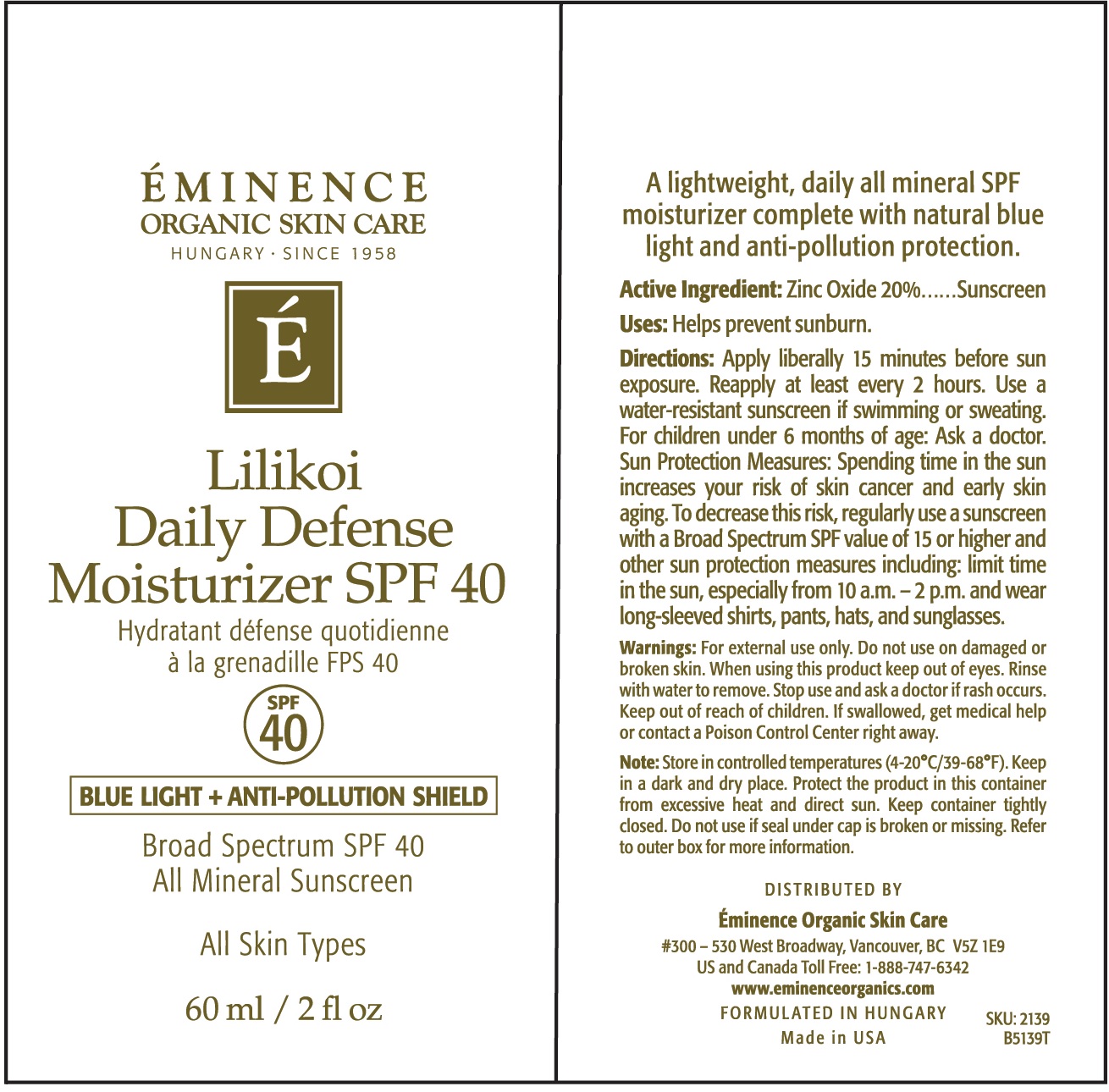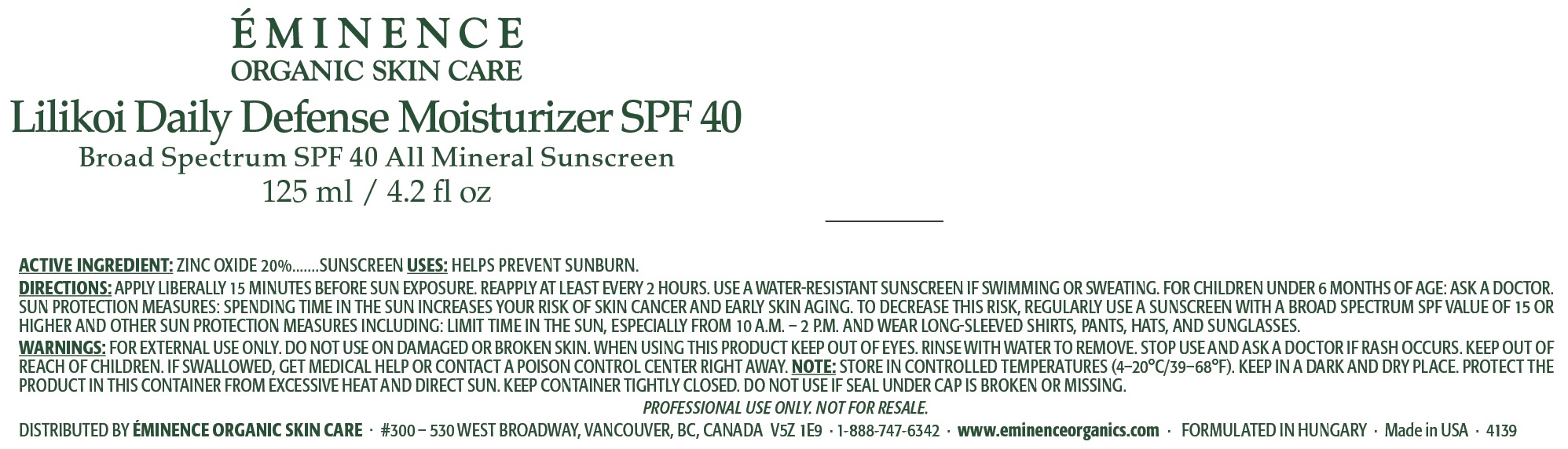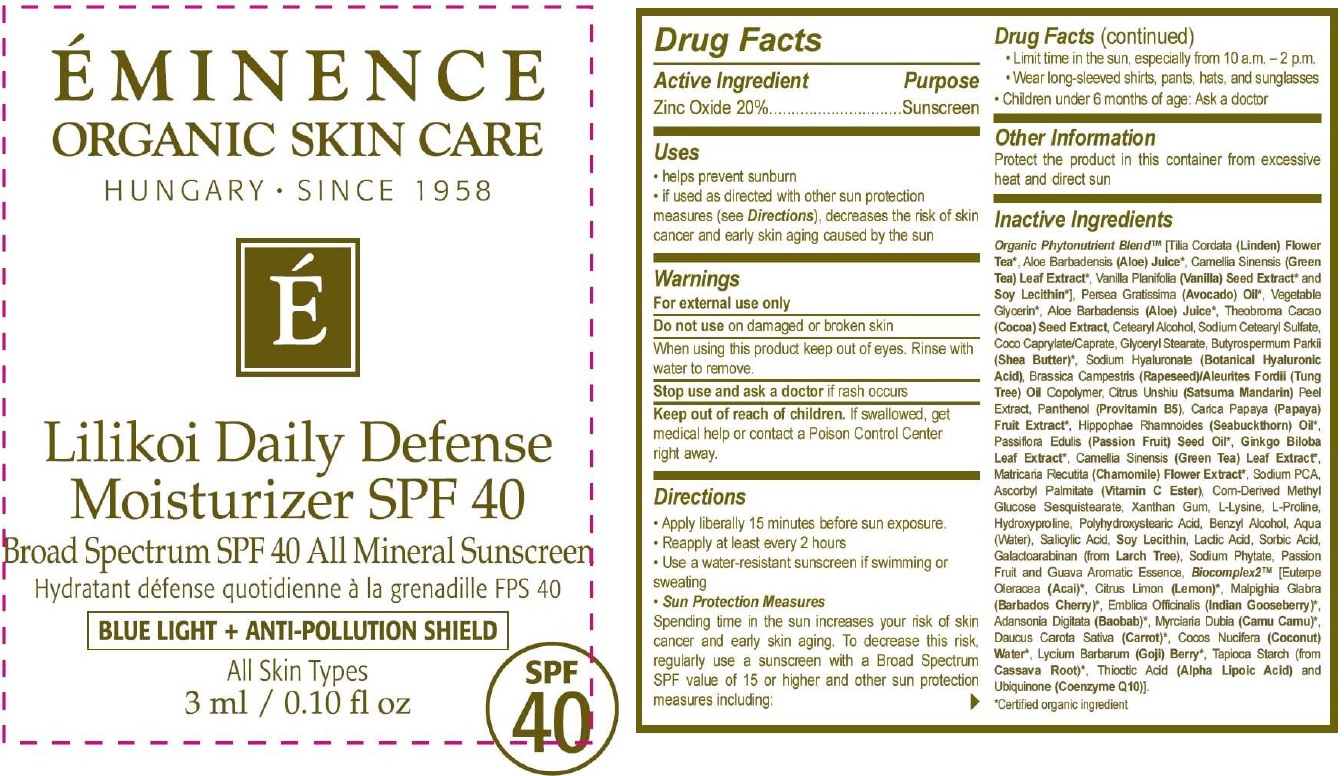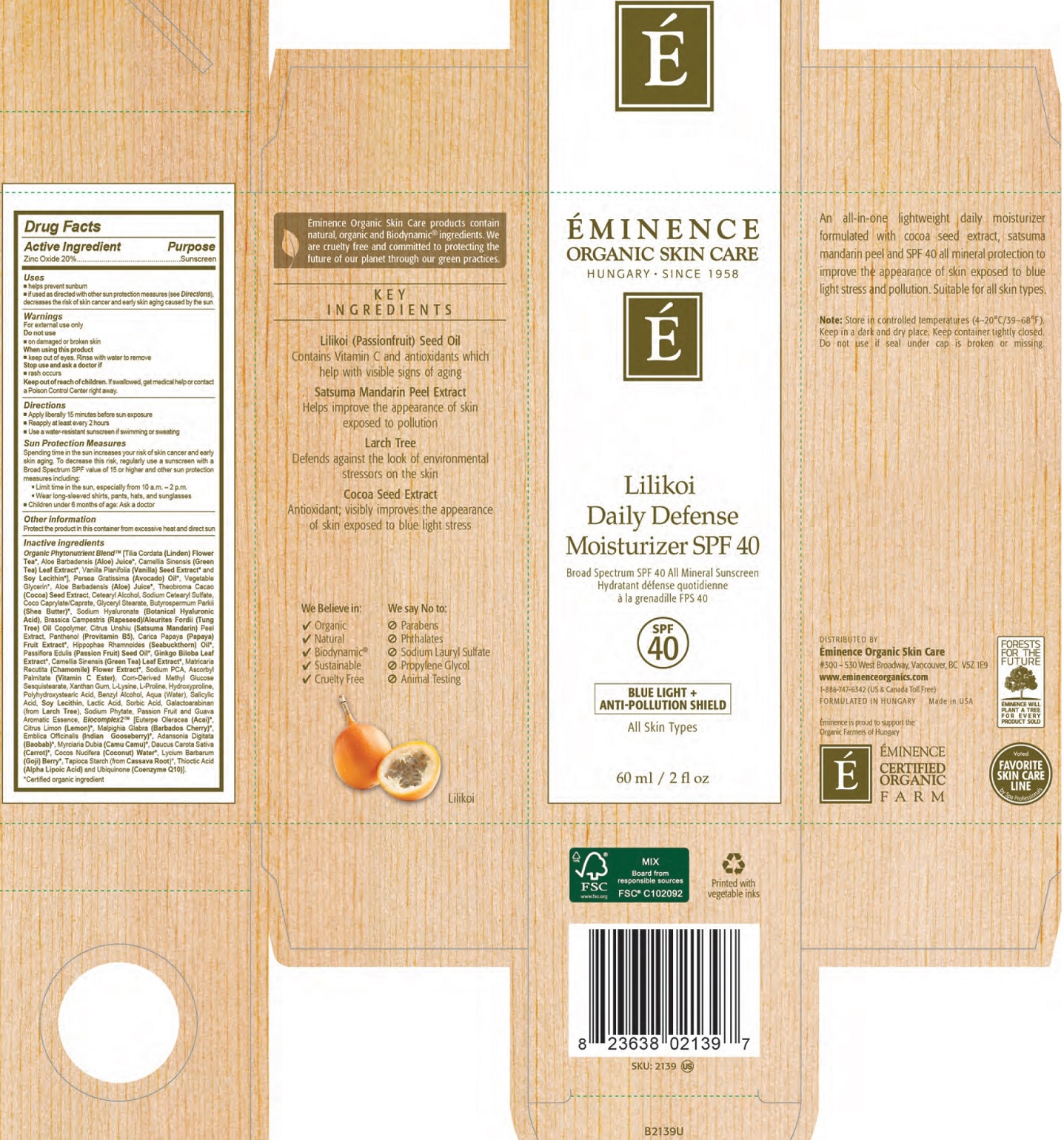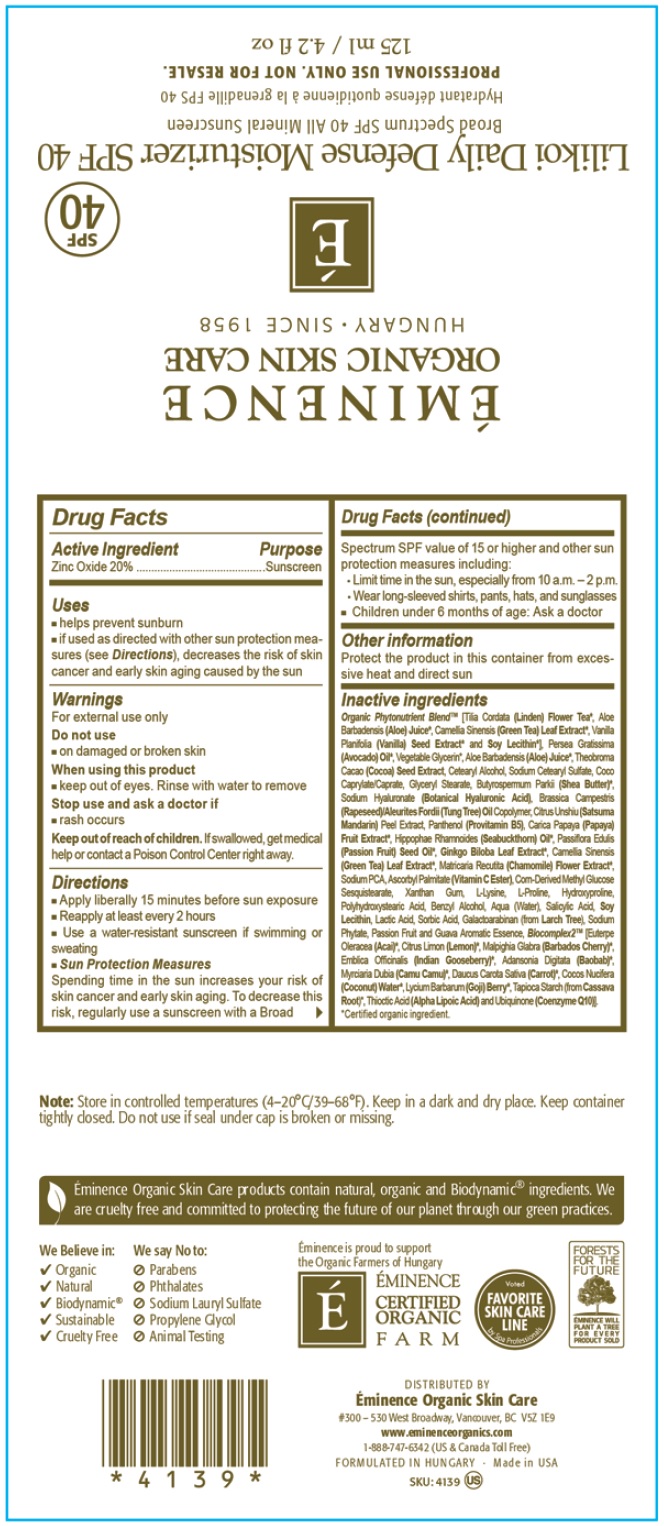 DRUG LABEL: Eminence Lilikoi Daily Defense Moisturizer SPF 40 Sunscreen
NDC: 15751-3501 | Form: CREAM
Manufacturer: Eminence Organic Skin Care
Category: otc | Type: HUMAN OTC DRUG LABEL
Date: 20231202

ACTIVE INGREDIENTS: ZINC OXIDE 200 mg/1 mL
INACTIVE INGREDIENTS: ALOE VERA LEAF; GREEN TEA LEAF; VANILLA BEAN; AVOCADO OIL; GLYCERIN; COCOA; CETOSTEARYL ALCOHOL; SODIUM CETOSTEARYL SULFATE; COCOYL CAPRYLOCAPRATE; GLYCERYL MONOSTEARATE; SHEA BUTTER; HYALURONATE SODIUM; SODIUM PYRROLIDONE CARBOXYLATE; TANGERINE PEEL; PANTHENOL; PAPAYA; PASSIFLORA EDULIS SEED OIL; GINKGO; CHAMOMILE; ASCORBYL PALMITATE; XANTHAN GUM; LYSINE; PROLINE; HYDROXYPROLINE; BENZYL ALCOHOL; WATER; SALICYLIC ACID; LECITHIN, SOYBEAN; LACTIC ACID; SORBIC ACID; GALACTOARABINAN; HEXASODIUM PHYTATE; LEMON; CARROT; COCONUT WATER; STARCH, TAPIOCA; THIOCTIC ACID; UBIDECARENONE

Eminence Lilikoi Daily Defense Moisturizer SPF 40 Sunscreen

Active Ingredient

Zinc Oxide 20%

Purpose

Sunscreen

Uses

- helps prevent sunburn
- if used as directed with other sun protection measures (see Directions), decreases the risk of skin cancer and early skin aging caused by sun

Warnings

For external use only

Do not use

- on damaged or broken skin

When using this product

- keep out of eyes. Rinse with water to remove

Stop use and ask a doctor if

- rash occurs

Keep out of reach of children.

If swallowed, get medical help or contact a Poison Control Center right away.

Directions

- Apply liberally 15 minutes before sun exposure
- Reapply at least every 2 hours
- Use a water-resistant sunscreen if swimming or sweating
- Sun Protection Measures Spending time in the sun increases your risk of skin cancer and early skin aging. To decrease this risk, regularly use a sunscreen with a Broad Spectrum SPF value of 15 or higher and other sun protection measures including:
- Limit time in the sun, especially from 10 a.m. - 2 p.m
- Wear long sleeved shirts, pants, hats and sunglasses
- Children under 6 months of age: Ask a doctor

Other information

Protect the product in this container from excessive heat and direct sun

Inactive Ingredients

Organic Phytonutrient Blen [Tila Cordata (Linden) Flower Tea*, Aloe Barbadensis (Aloe) Juice, Camellia Sinensis (Green Tea) Leaf Extract*, Vanilla Planifolia (Vanilla) seed Extract* and Soy Lecithin*), Persea Gratissima (Avocado) Oil*, Vegetable Glycerin*, ALoe Barbadensis (Aloe) Juice*, Theobroma Cacao (Cocoa) Seed Extract, Cetearyl Alcohol, Sodium Cetearyl Sulfate, Coco Caprylate/Caprate, Glyceryl Stearate, Butyrospermum Parkii (Shea Butter)*, Sodium Hyaluronate (Botanical Hyaluronic Acid), Brassica Campestris (Rapeseed)/Aleurites Fordii (Tung Tree) Oil Copolymer, Citrus Unshiu (Satsuma Mandarin) Peel Extract, Panthenol (Provitamin B5), Carica Papaya (Papaya) Fruit Extract, Hippophae Rhamnoides (Seabuckthorn) Oil*, Passiflora Edulis (Passion Fruit) Seed Oil*, Ginkgo Biloba Leaf Extract, Camellis Sinensis (Green Tea) Leaf Extract, Matricaria Recutita (Chamomile) Flower Extract*, Sodium PCA, Ascorbyl Palmitate (Vitamin C Ester), Corn-Derived Methyl Glucose Sesquistearate, Xanthan Gum, L-Lysine, L-Proline, Hydroxyproline, Polyhydroxystearic Acid, Benzyl Alcohol, Aqua (Water), Salicylic Acid, Soy Lecithin, Lactic Acid, Sorbic Acid, Galactoarabinan (from Larch Tree), Sodium Phytate, Passion Fruit and Guava Aromatic Essence, Blocomplex2 [Euterpe Oleracea (Acai)*, Citrus Limon (Lemon)*, Malpighia Glabra (Barbados Cherry)*, Emblica Officinalis (Indian Gooseberry)*, Adansonia Digitata (Baobab)*, Myrciaria Dubia (Camu Camu)*, Daucus Carota Daucus Carota Sativa (Carrot)*, Cocos Nucifera (Coconut) Water*, Lycium Barbarum (Goji) Berry*, Tapioca Starch (from Cassava Root)*, Thioctic Acid (Alpha Lipoic Acid) and Ubiquinone (Coenzyme Q10)].

Certified organic ingredient

Note

Store in controlled temperatures (4–20°C/39–68°F). Keep in a dark and dry place. Keep container tightly closed. Do not use if seal under cap is broken or missing.